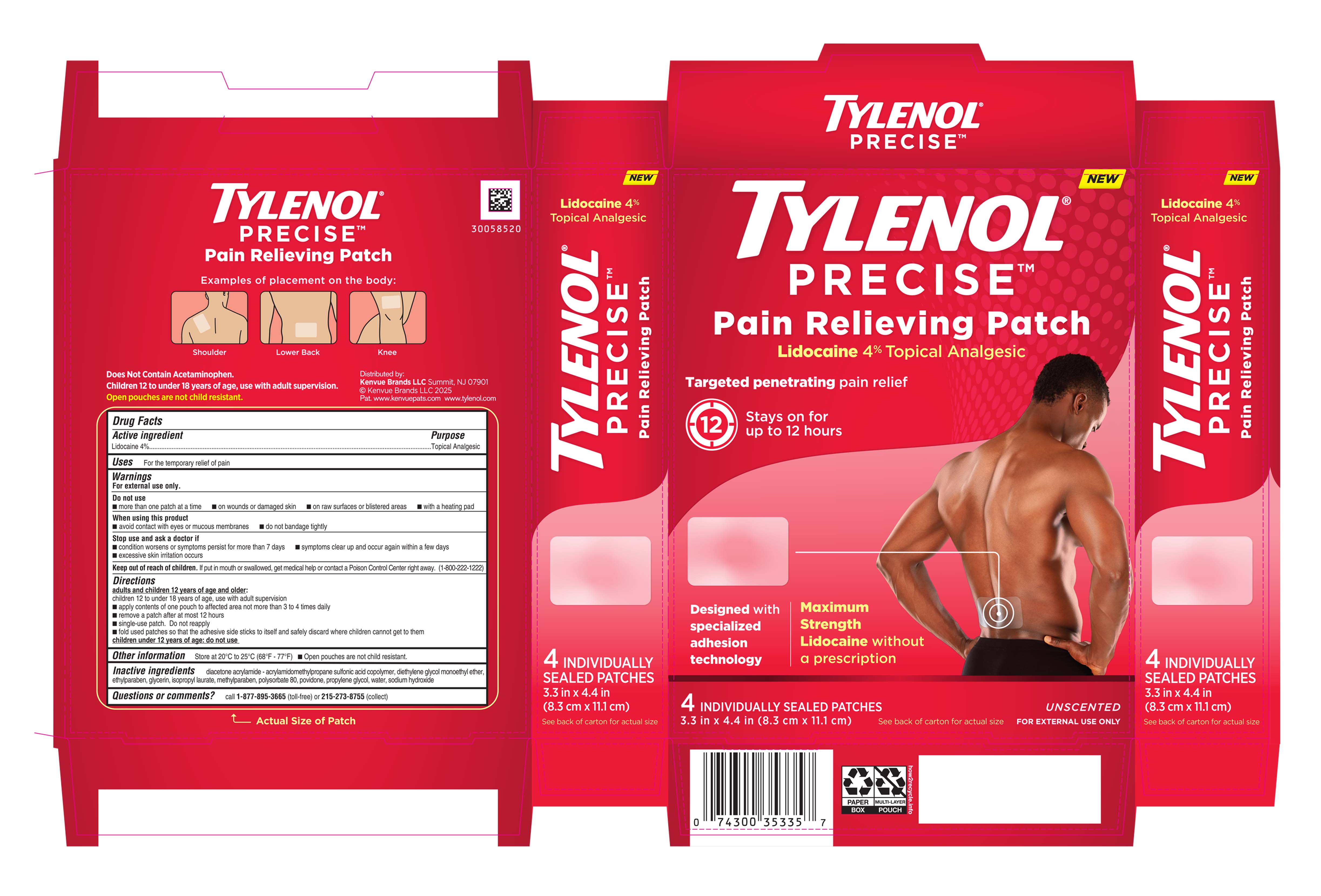 DRUG LABEL: Tylenol Precise Pain Relieving Lidocaine 4%
NDC: 69968-0927 | Form: PATCH
Manufacturer: Kenvue Brands LLC
Category: otc | Type: HUMAN OTC DRUG LABEL
Date: 20250930

ACTIVE INGREDIENTS: LIDOCAINE 40 mg/1 1
INACTIVE INGREDIENTS: DIETHYLENE GLYCOL MONOETHYL ETHER; ETHYLPARABEN; GLYCERIN; ISOPROPYL LAURATE; METHYLPARABEN; POLYSORBATE 80; POVIDONE; PROPYLENE GLYCOL; WATER; SODIUM HYDROXIDE

Tylenol Precise Pain Relieving Patch Lidocaine 4%

Drug Facts

Active ingredient

Lidocaine 4%

Purpose

Topical Analgesic

Uses

For the temporary relief of pain

Warnings

For external use only.

Do not use

- more than one patch at a time
- on wounds or damaged skin
- on raw surfaces or blistered areas
- with a heating pad

When using this product

- avoid contact with eyes or mucous membranes
- do not bandage tightly

Stop use and ask a doctor if

- condition worsens or symptoms persist for more than 7 days
- symptoms clear up and occur again within a few days
- excessive skin irritation occurs

Keep out of reach of children. If put in mouth or swallowed, get medical help or contact a Poison Control Center right away. (1-800-222-1222)

Directions

adults and children 12 years of age and older:

children 12 to under 18 years of age, use with adult supervision

- apply contents of one pouch to affected area not more than 3 to 4 times daily
- remove a patch after at most 12 hours
- single-use patch. Do not reapply
- fold used patches so that the adhesive side sticks to itself and safely discard where children cannot get to them

children under 12 years of age: do not use

Other Information

Store at 20°C to 25°C (68°F - 77°F) ■ Open pouches are not child resistant.

Inactive Ingredients

diacetone acrylamide - acrylamidomethylpropane sulfonic acid copolymer, diethylene glycol monoethyl ether, ethylparaben, glycerin, isopropyl laurate, methylparaben, polysorbate 80, povidone, propylene glycol, water, sodium hydroxide

Questions or comments?

call 1-877-895-3665 (toll-free) or 215-273-8755 (collect)

Distributed by:
Kenvue Brands LLC
Summit, NJ 07901

PRINCIPAL DISPLAY PANEL - Tylenol Patch Label

NEW

TYLENOL®

PRECISETM

Pain Relieving Patch

Lidocaine 4% Topical Analgesic

Targeted penetrating pain relief

12

Stays on for

up to 12 hours

Designed with

specialized

adhesion

technology

Maximum

Strength

Lidocaine without

a prescription

4 INDIVIDUALLY SEALED PATCHES

3.3 in X 4.4 in (8.3 cm X 11.1 cm)

See back of carton for actual size

UNSCENTED

FOR EXTERNAL USE ONLY